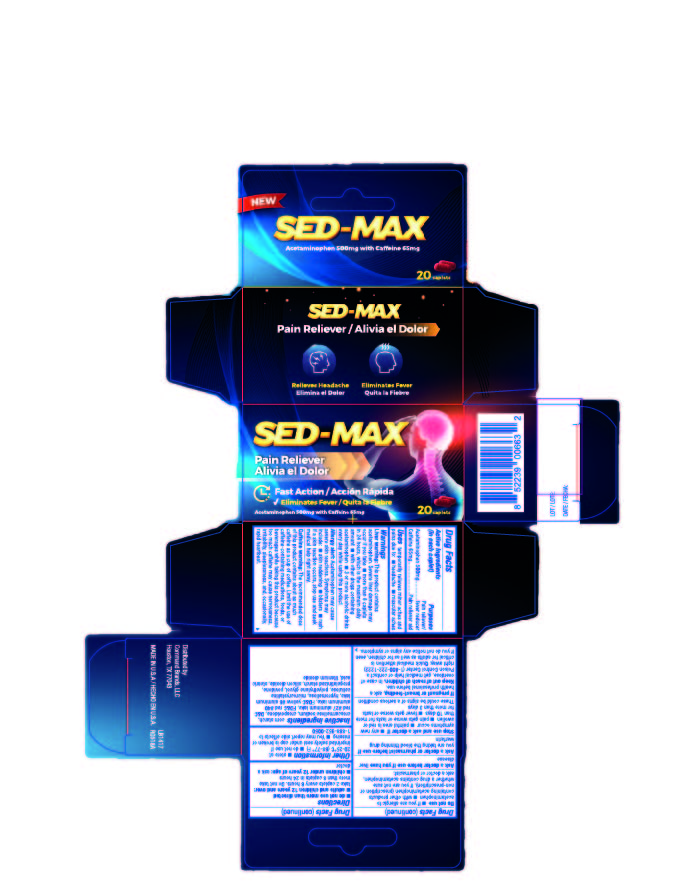 DRUG LABEL: SED-MAX
NDC: 69197-029 | Form: TABLET, COATED
Manufacturer: Command Brands, LLC
Category: otc | Type: HUMAN OTC DRUG LABEL
Date: 20170119

ACTIVE INGREDIENTS: ACETAMINOPHEN 500 mg/1 1; CAFFEINE 65 mg/1 1
INACTIVE INGREDIENTS: STARCH, CORN; CROSCARMELLOSE; CROSPOVIDONE; D&C RED NO. 27 ALUMINUM LAKE; FD&C RED NO. 40; FD&C YELLOW NO. 6; HYPROMELLOSES; MICROCRYSTALLINE CELLULOSE; POLYETHYLENE GLYCOL, UNSPECIFIED; POVIDONE; SILICON DIOXIDE; STEARIC ACID; TITANIUM DIOXIDE

029 - SED-MAX

Active ingredient(s)

Acetaminophen 500mg

Caffeine 65mg

Purpose

Pain reliever/fever reducer

Pain reliever aid

Uses

temporary relief of minor aches and pains due to:

■ headache

■ muscular aches

Warnings

Liver warning: This product contains acetaminophen. Severe liver damage may occur if you

■ take more than 8 caplets in 24 hours, which is the maximum daily amount

■ taken with other drugs containing acetaminophen

■ adult has 3 or more alcoholic drinks every day while using this product

Allergy alert: Acetaminophen may cause severe skin reactions. Symptoms may include:

■ skin reddening

■ blisters

■ rash

If a skin reaction occurs, stop use and seek medical help right away.

Caffeine warning: The recommended dose of this product contains about as much caffeine as a cup of coffee. Limit the use of caffeine-containing medications, foods, or beverages while taking this product because too much caffeine may cause nervousness, irritability, sleeplessness, and, occasionally, rapid heart beat.

Do not use

■ if you are allergic to acetaminophen

■ with other products containing acetaminophen (prescription or nonprescription).

If you are not sure whether a drug contains acetaminophen, ask a doctor or pharmacist.

Ask a doctor before use if you have

liver disease

Ask a doctor or pharmacist before use if

you are taking the blood thinning drug warfarin

Stop use and ask a doctor if

■ any new symptoms occur

■ painful area is red or swollen

■ pain gets worse or lasts more than 10 days

■ fever gets worse or lasts more than 3 days

These could be signs of a serious skin condition

Pregnancy/Breastfeeding

If pregnant or breast-feeding, ask a health professional before use.

Keep out of reach of children

In case of overdose, get medical help or contact a Poison Control Center (1-800-222-1222) right away. Quick medical attention is critical for adults as well as for children, even if you do not notice any signs or symptoms.

Directions

■ do not use more than directed

■ Adults and children 12 years and over: take 2 caplets every 6 hours. Do not take more than 8 caplets in 24 hours

■ Children under 12 years of age: ask a doctor

Other information

■ store at 20-25C (68-77F)

■ do not use if imprinted safety seal under cap is broken or missing

■you may report side effects to 1-888-952-0050

Inactive ingredients

corn starch, croscarmellose, crospovidone, D&C red #27 aluminum lake, FD&C red #40 aluminum lake, FD&C yellow #6 aluminum lake, hypromellose, microcrystalline cellulose, polyethylene glycol, povidone, pregelatinized starch, silicon dioxide, stearic acid, titanium dioxide

Principal Display Panel

Sedmax